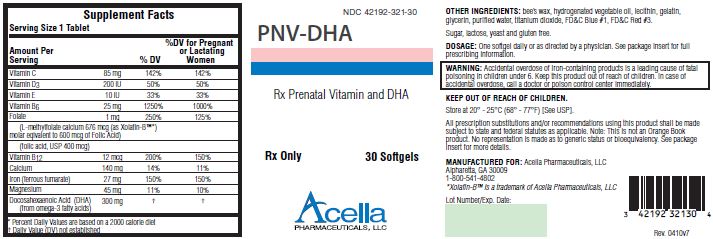 DRUG LABEL: PNV-DHA
NDC: 42192-321 | Form: CAPSULE, GELATIN COATED
Manufacturer: Acella Pharmaceuticals, LLC
Category: prescription | Type: HUMAN PRESCRIPTION DRUG LABEL
Date: 20240115

ACTIVE INGREDIENTS: ASCORBIC ACID 85 [iU]/1 1; CHOLECALCIFEROL 200 [iU]/1 1; .ALPHA.-TOCOPHEROL ACETATE, DL- 10 [iU]/1 1; PYRIDOXINE 25 [iU]/1 1; FOLIC ACID 1 mg/1 1; CYANOCOBALAMIN 12 ug/1 1; CALCIUM 140 mg/1 1; FERROUS FUMARATE 27 mg/1 1; MAGNESIUM 45 mg/1 1; DOCONEXENT 300 mg/1 1
INACTIVE INGREDIENTS: CARNAUBA WAX; CORN OIL; LECITHIN, SOYBEAN; GELATIN; GLYCERIN; WATER; TITANIUM DIOXIDE; FD&C BLUE NO. 1; FD&C RED NO. 3

PNV-DHA

Rx Only

DESCRIPTION

DESCRIPTION: PNV-DHA is a prescription prenatal/postnatal multivitamin/mineral/essential fatty acid softgel. Each softgel is blue in color, opaque and imprinted with “BP 321” on one side.

Supplement Facts
Serving Size 1 Tablet
Amount Per Serving |  | % DV | %DV for Pregnant or Lactating Women
Vitamin C | 85 mg | 142% | 142%
Vitamin D3 | 200 IU | 50% | 50%
Vitamin E | 10 IU | 33% | 33%
Vitamin D6 | 25 mg | 1250% | 1000%
Folate | 1 mg | 250% | 125%
(L-methylfolate calcium 676 mcg (as Xolafin-B™ [Percent Daily Values are based on a 2000 calorie diet])
molar equivalent to 600 mcg of Folic Acid)
(folic acid, USP 400 mcg)
Vitamin B12 | 12 mcg | 200% | 150%
Calcium | 140 mg | 14% | 11%
Iron (ferrous fumarate) | 27 mg | 150% | 150%
Magnesium | 45 mg | 11% | 10%
Docosahexaenoic Acid (DHA) (from omega-3 fatty acids) | 300 mg | [Daily Value (DV) not established]

INACTIVE INGREDIENT

OTHER INGREDIENTS: bee’s wax, hydrogenated vegetable oil, lecithin, gelatin, glycerin, purified water, titanium dioxide, FD&C Blue #1, FD&C Red #3.

INDICATIONS AND USAGE

INDICATIONS: PNV-DHA is a multivitamin/multimineral nutritional supplement indicated for use in the dietary management of patients with nutritional deficiencies or are in need of nutritional supplementation.

CONTRAINDICATIONS

CONTRAINDICATIONS: This product is contraindicated in patients with a known hypersensitivity to any of the ingredients.

WARNINGS

WARNING: Ingestion of more than 3 grams of omega-3 fatty acids (such as DHA) per day has been shown to have potential antithrombotic effects, including an increased bleeding time and International Normalized Ratio (INR). Administration of omega-3 fatty acids should be avoided in patients taking anticoagulants and in those known to have an inherited or acquired predisposition to bleeding.

BOXED WARNING

WARNING: Accidental overdose of iron-containing products is a leading cause of fatal poisoning in children under 6. Keep this product out of reach of children. In case of accidental overdose, call a doctor or poison control center immediately.

PRECAUTIONS

PRECAUTIONS: Folic acid alone is improper therapy in the treatment of pernicious anemia and other megaloblastic anemias where Vitamin B12 is deficient. Folic acid in doses above 1.0 mg daily may obscure pernicious anemia in that hematologic remission can occur while neurological manifestations progress.

ADVERSE REACTIONS

ADVERSE REACTIONS: Allergic sensitization has been reported following both oral and parenteral administration of folic acid.

DOSAGE AND ADMINISTRATION: Before, during and/or after pregnancy, one softgel daily or as directed by a physician.

HOW SUPPLIED

HOW SUPPLIED: PNV-DHA is supplied in child-resistant bottles of 30 softgels (NDC# 42192-321-30).

Store at 20° - 25°C (68° - 77°F); excursions permitted to 15° - 30°C (59° - 86°F) [See USP Controlled Room Temperature.]

KEEP THIS AND ALL MEDICATIONS OUT OF THE REACH OF CHILDREN.

All prescription substitutions and/or recommendations using this product shall be made subject to state and federal statutes as applicable. Please note: this is not an Orange Book product and has not been subjected to FDA therapeutic equivalency or other equivalency testing. No representation is made as to generic status or bioequivalency. Each person recommending a prescription substitution using this product shall make such recommendations based on each such person’s professional opinion and knowledge, upon evaluating the active ingredients, excipients, inactive ingredients and chemical information provided herein.

MANUFACTURED FOR: Acella Pharmaceuticals, LLC
9005 Westside Parkway
Alpharetta, GA 30009
1-800-541-4802
Rev. 04/10v6

*Xolafin-B™ is a trademark of Acella Pharmaceuticals, LLC

PRINCIPAL DISPLAY PANEL - 30 Softgel Tablets

NDC 42192-321-30

PNV-DHA

Rx Prenatal Vitamin and DHA

Rx Only 30 Softgels

Acella
PHARMACEUTICALS, LLC